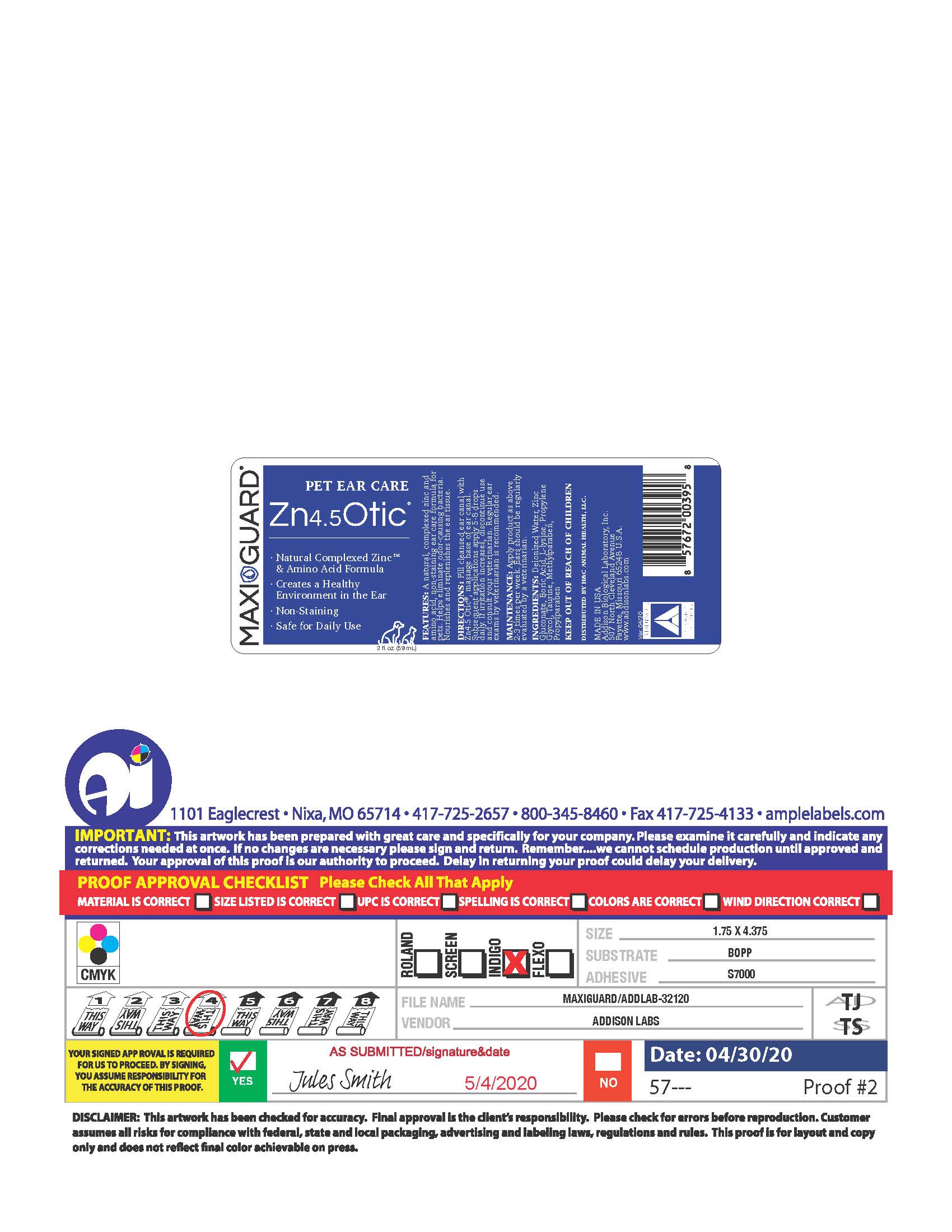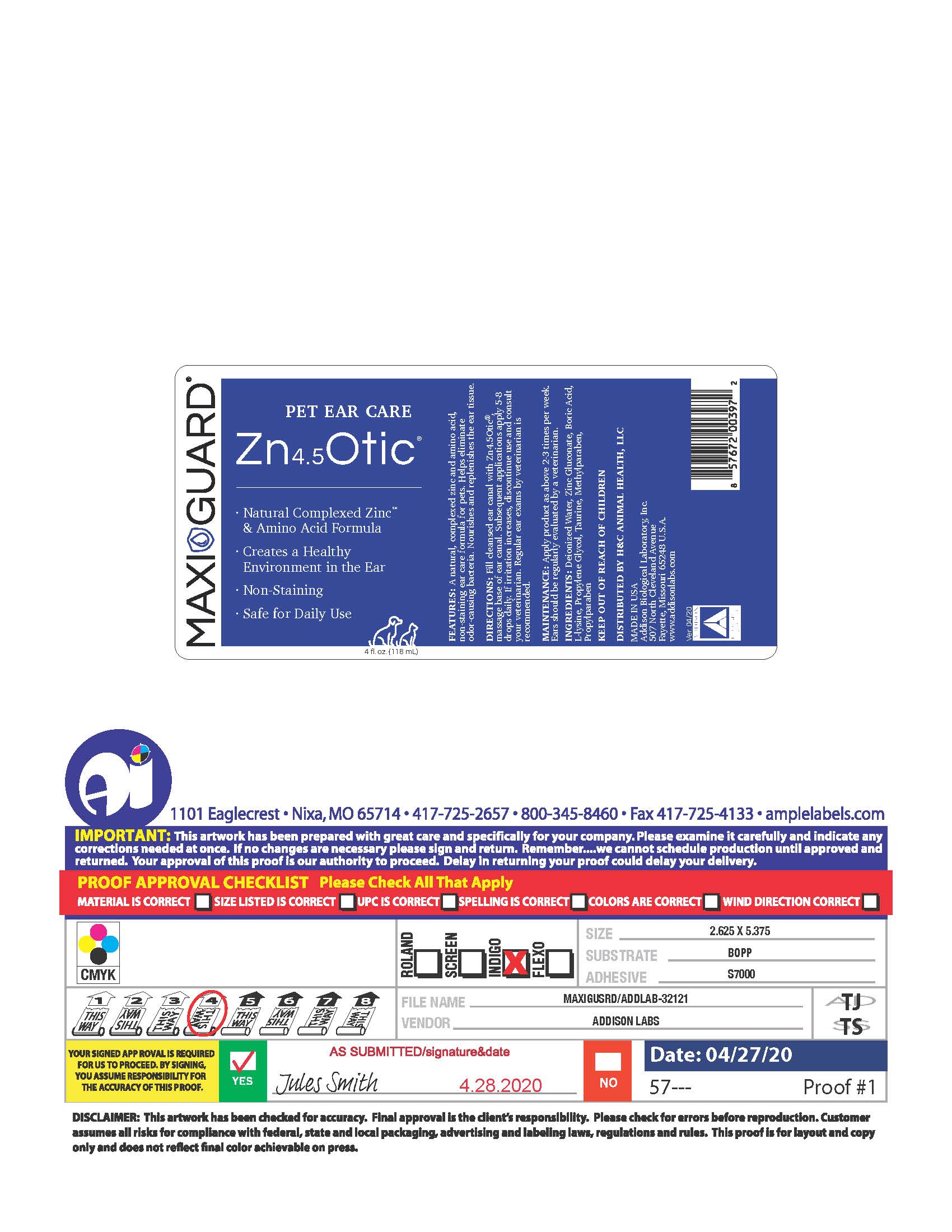 DRUG LABEL: Zn4.5 Otic
NDC: 86137-7609 | Form: SOLUTION
Manufacturer: H&C Animal Health
Category: animal | Type: OTC ANIMAL DRUG LABEL
Date: 20251201

ACTIVE INGREDIENTS: ZINC GLUCONATE .011 g/1 mL
INACTIVE INGREDIENTS: WATER; TAURINE; METHYLPARABEN; PROPYLPARABEN; LYSINE; BORIC ACID; PROPYLENE GLYCOL

Zn4.5 Otic

INDICATIONS:

A natural, complexed zinc and amino acid, non-staining ear care formula for pets. Helps eliminate odor-causing bacteria. Nourishes and replenishes the ear tissue.

INFORMATION FOR OWNERS/CAREGIVERS

- Natural Complexed Zinc and Amino Acid formula.
- Creates a Healthy Environment in the Ear.
- Non-Staining
- Safe for Daily Use

Keep out of reach of children.

DIRECTIONS:

Fill cleansed ear canal with Zn4.5Otic, massage base of ear canal. Subsequent applications, apply 5-8 drops daily. If irritation increases, discontinue use and consult your veterinarian. Regular ear exams by veterinarian is recommended.

ROUTE, METHOD AND FREQUENCY OF ADMINISTRATION

MAINTENANCE:

Apply product as above 2-3 times per week. Ears should be regularly evaluated by a veterinarian.

INACTIVE INGREDIENT

INGREDIENTS:

Deionized Water, Zinc Gluconate, Boric Acid, L-Lysine, Propylene Glycol, Taurine, Methylparaben, Propylparaben.

DISTRIBUTED BY H&C ANIMAL HEALTH , LLC.

MADE IN THE U.S.A.

Addison Biological Laboratory, Inc.

507 North Cleveland Avenue
Fayette, Missouri 65248 U.S.A.
www.addisonlabs.com
Rev. 04/20

Package label, display panel

MAXI/GUARD®
Zn4.5Otic®
• Natural Complexed Zinc and Amino Acid formula.
• Creates a Healthy Environment in the Ear.
• Non-Staining
• Safe for Daily Use
2 FL. OZ. (59mL)
FEATURES:
A natural, complexed zinc and amino acid, non-staining ear care formula for pets. Helps eliminate odor-causing bacteria. Nourishes and replenishes the ear tissue. Nourishes and replenishes
DIRECTIONS:
Fill cleansed ear canal with Zn4.5Otic, massage base of ear canal. Subsequent applications, apply 5-8 drops daily. If irritation increases, discontinue use and consult your veterinarian. Regular ear exams by veterinarian is recommended.
MAINTENANCE:
Apply product as above 2-3 times per week. Ears should be regularly evaluated by a veterinarian.
INGREDIENTS:
Deionized Water, Zinc Gluconate, Boric Acid,
L-Lysine, Propylene Glycol,
Taurine, Methylparaben, Propylparaben.
KEEP OUT OF REACH OF CHILDREN.
DISTRIBUTED BY H&C ANIMAL HEALTH , LLC.
Addison Biological Laboratory, Inc.
507 North Cleveland Avenue
Fayette, Missouri 65248 U.S.A.
www.addisonlabs.com
Rev. 04/20

Package label , display panel

MAXI/GUARD®
Zn4.5Otic®
• Natural Complexed Zinc and Amino Acid formula.
• Creates a Healthy Environment in the Ear.
• Non-Staining
• Safe for Daily Use
4 FL. OZ. (118mL)
FEATURES:
A natural, complexed zinc and amino acid, non-staining ear care formula for pets. Helps eliminate odor-causing bacteria. Nourishes and replenishes the ear tissue. Nourishes and replenishes
DIRECTIONS:
Fill cleansed ear canal with Zn4.5Otic, massage base of ear canal. Subsequent applications, apply 5-8 drops daily. If irritation increases, discontinue use and consult your veterinarian. Regular ear exams by veterinarian is recommended.
MAINTENANCE:
Apply product as above 2-3 times per week. Ears should be regularly evaluated by a veterinarian.
INGREDIENTS:
Deionized Water, Zinc Gluconate, Boric Acid,
L-Lysine, Propylene Glycol,
Taurine, Methylparaben, Propylparaben.
KEEP OUT OF REACH OF CHILDREN.
DISTRIBUTED BY H&C ANIMAL HEALTH , LLC.
Addison Biological Laboratory, Inc.
507 North Cleveland Avenue
Fayette, Missouri 65248 U.S.A.
www.addisonlabs.com
Rev. 04/20